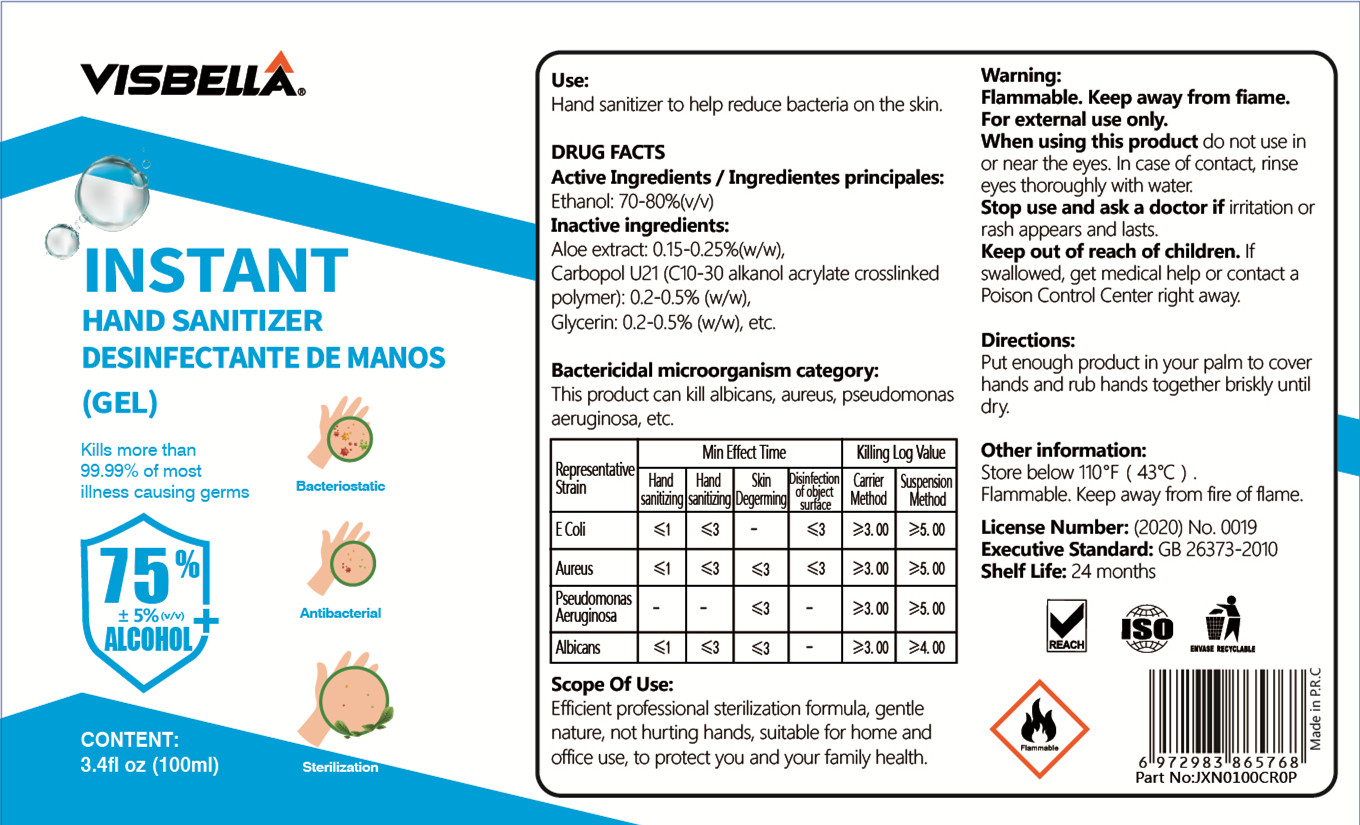 DRUG LABEL: VISBELLA instant hand sanitizer desinfectante de manos
NDC: 40760-001 | Form: GEL
Manufacturer: Huzhou Guoneng New Material Co., Ltd.
Category: otc | Type: HUMAN OTC DRUG LABEL
Date: 20200708

ACTIVE INGREDIENTS: ALCOHOL 75 mL/100 mL
INACTIVE INGREDIENTS: GLYCERIN; ALOE; CARBOMER HOMOPOLYMER, UNSPECIFIED TYPE

PURPOSE

Disinfection
Sterilization
No Rinseing

ACTIVE INGREDIENT

alcohol

INACTIVE INGREDIENT

aloe extract，carbopol U21 （C10-30 alkanol acrylate crosslinked polymer），glycerin

keep out of reach of children

INDICATIONS AND USAGE

Put enough product in your palm to cover hands and rub hands together briskly until dry.

WARNINGS

For external use only.
When using this product do not use in or near the eyes. In case of contact, rinse eyes thoroughly with water.
Stop use and ask a doctor if iritation or rash appears and lasts.
Keep out of reach of children.
If swallowed, get medical help.

DOSAGE AND ADMINISTRATION

Store below 110°F (43°C).
Flammable. Keep away from fire of flame.